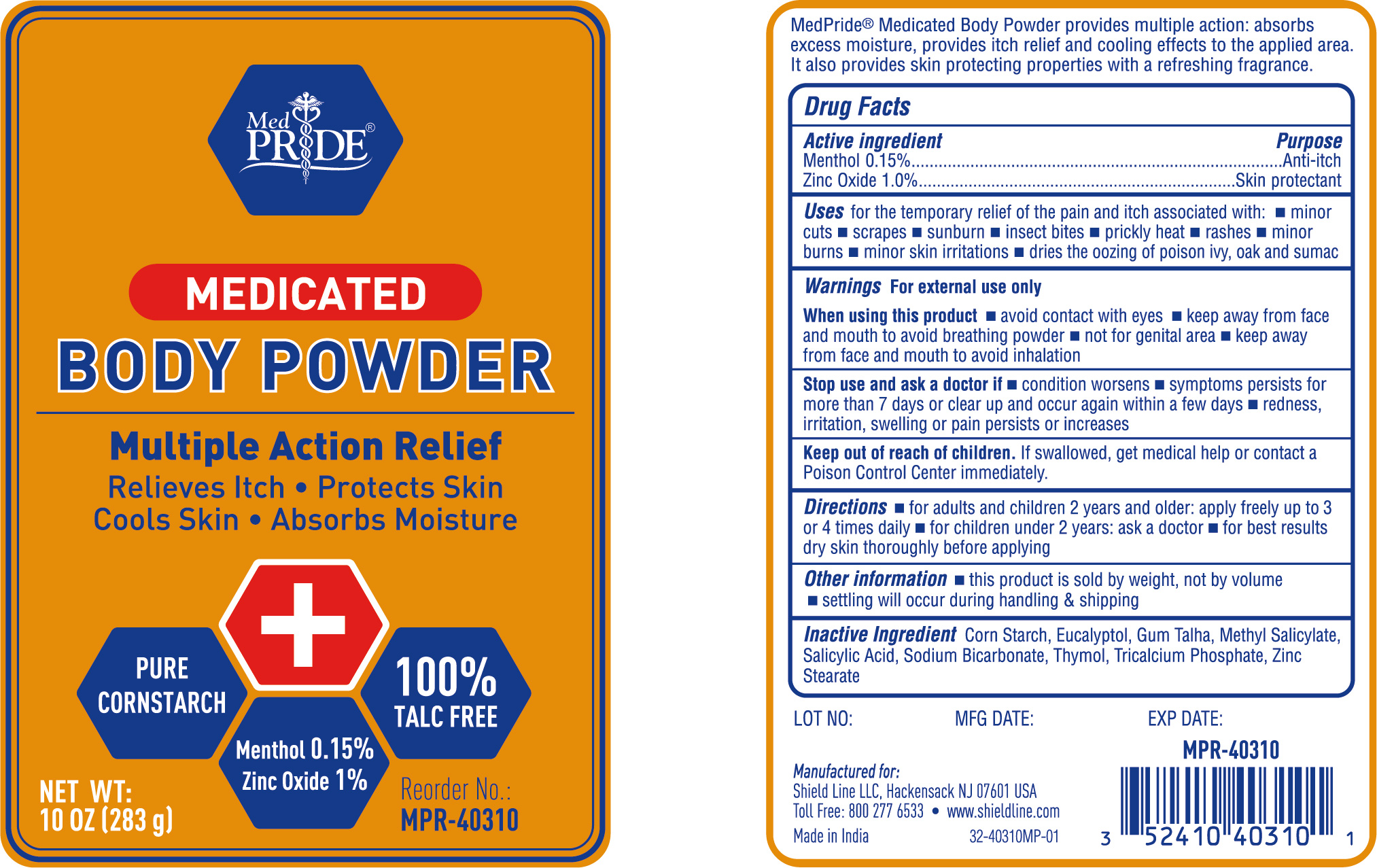 DRUG LABEL: MedPride Medicated Body Powder
NDC: 52410-4031 | Form: POWDER
Manufacturer: Shield Line LLC
Category: otc | Type: HUMAN OTC DRUG LABEL
Date: 20250815

ACTIVE INGREDIENTS: MENTHOL 0.15 g/100 g; ZINC OXIDE 1 g/100 g
INACTIVE INGREDIENTS: SODIUM BICARBONATE; STARCH, CORN; GUM TALHA; EUCALYPTOL; METHYL SALICYLATE; SALICYLIC ACID; THYMOL; ZINC STEARATE; TRICALCIUM PHOSPHATE

MedPride Medicated Body Powder

Drug Facts Active Ingredients

Menthol 0.15 %

Zinc Oxide 1.0%

Purpose

Anti-itch

Skin Protectant

Uses

for the temporary relief of the pain and itch associated with

- minor cuts
- scrapes
- sunburn
- insect bites
- prickly heat
- rashes
- minor burns
- minor skin irritations
- dries the oozing of poison ivy, oak and sumac.

Keep out of reach of children. In case of accidential ingestion, get medical help or contact a Poison Control Center right away.

Warnings

For external use only

When usin this product

- Avoid contact with eyes.
- Keep away from face and mouth to avoid inhalation
- Not for genital area.

Stop use and ask a doctor if

- condition worsens
- symptoms do not get better within 7 days or clear up and occur again within a few days

Directions

- adults and children 2 years and older, apply freely up to 3 or 4 times daily
- under 2 years: ask a doctor before using
- for best results, dry skin thoroughly before use

Inactive Ingredients

Corn Starch, Eucalyptol, Gum Talha, Methyl Salicylate, Salicylic Acid, Sodium Bicarbonate, Thymol, Tricalcium Phosphate, Zinc Stearate